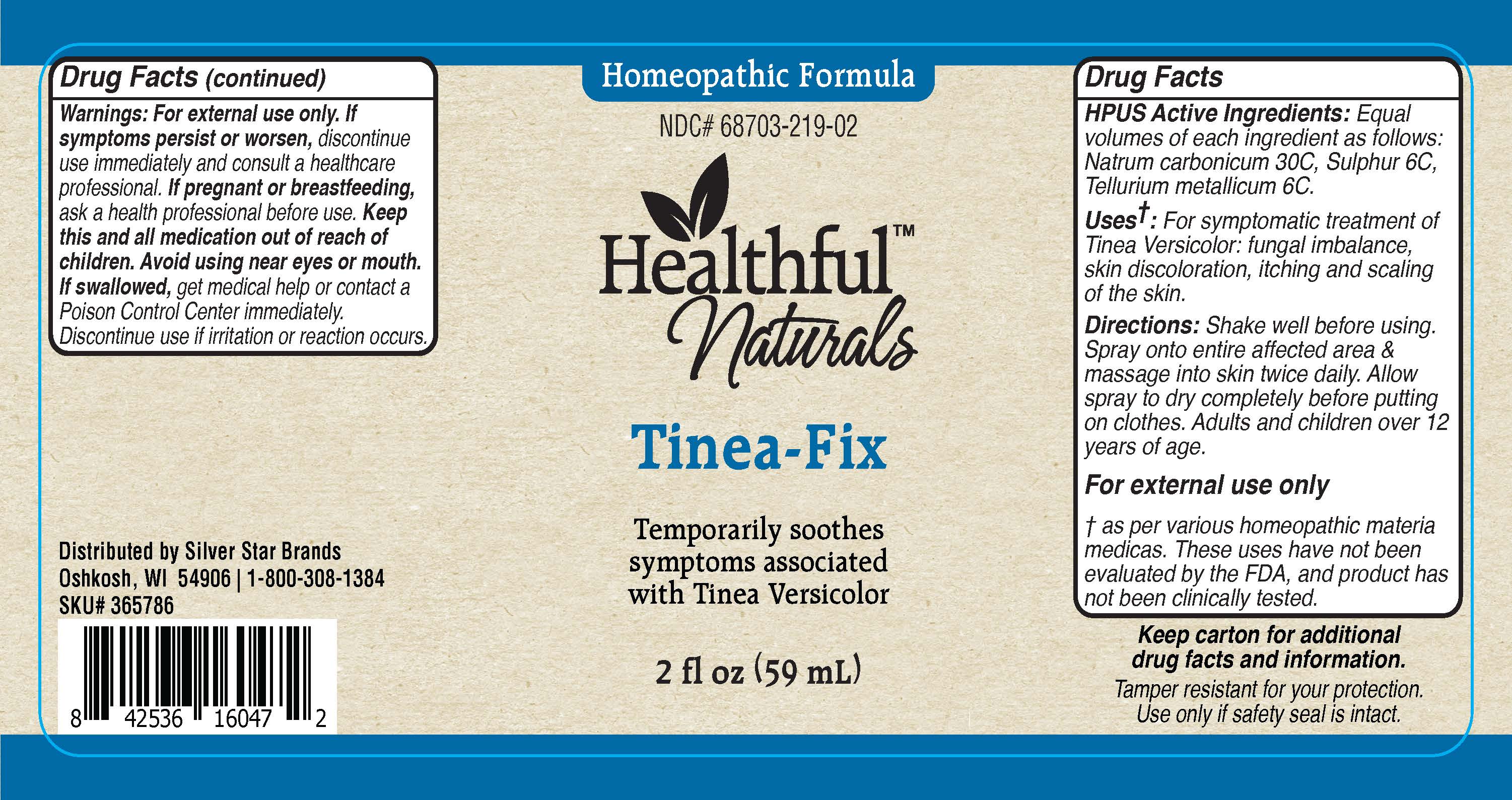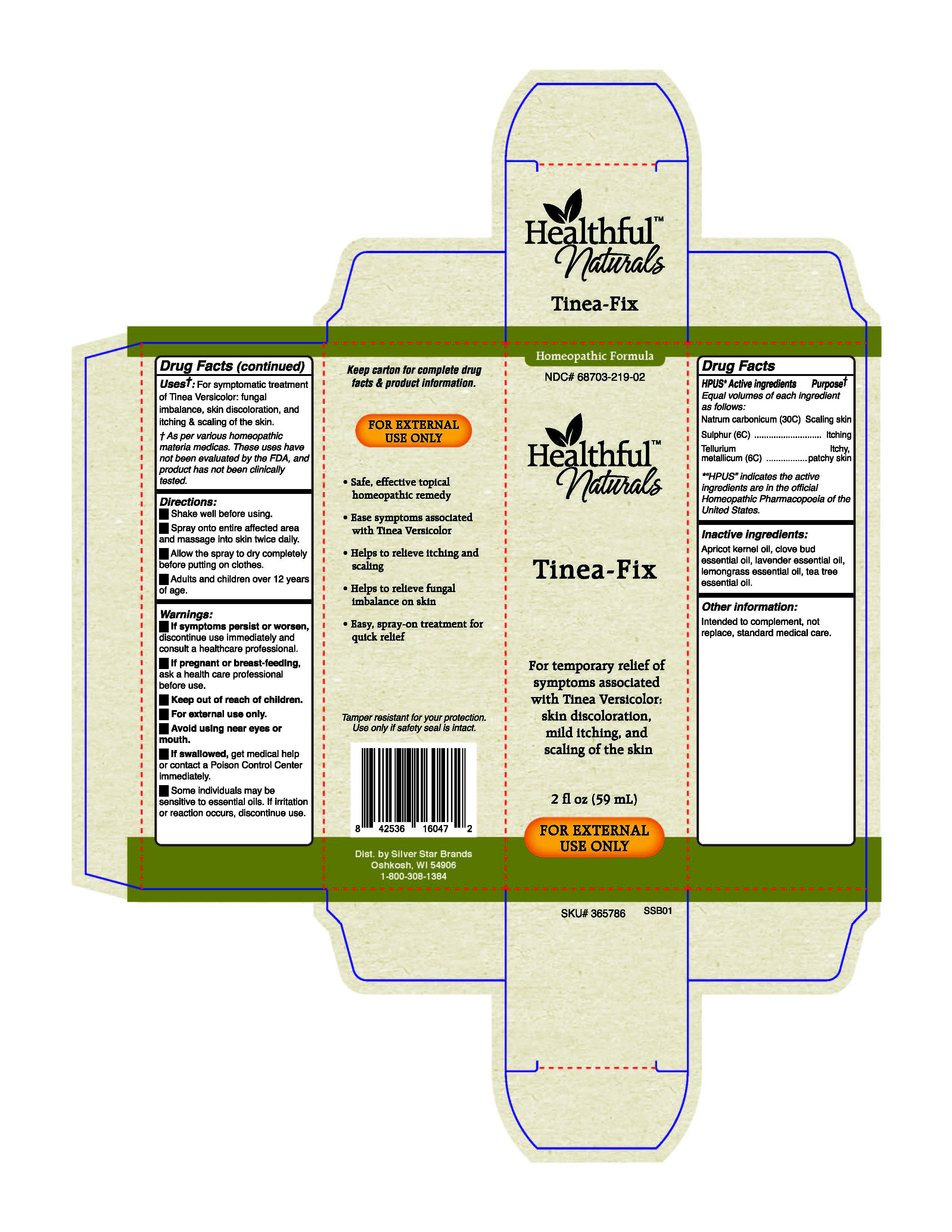 DRUG LABEL: Tinea-Fix
NDC: 68703-219 | Form: SPRAY
Manufacturer: Silver Star Brands
Category: homeopathic | Type: HUMAN OTC DRUG LABEL
Date: 20230304

ACTIVE INGREDIENTS: SULFUR 6 [hp_C]/59 mL; TELLURIUM 6 [hp_C]/59 mL; SODIUM CARBONATE 30 [hp_C]/59 mL
INACTIVE INGREDIENTS: APRICOT KERNEL OIL; CLOVE OIL; TEA TREE OIL; WEST INDIAN LEMONGRASS OIL; LAVENDER OIL

Healthful™ Naturals Tinea-Fix - 59 ml

HPUS* Active ingredients - Equal volumes of each ingredient as follows: Natrum cardonicum (30C), Sulphur (6C), Tellurium metallicum (6C).

*"HPUS" indicates the active ingredients are in the official Homeopathic Pharmacopoeia of the United States.

Uses*

Uses+: For symptomatic treatment of Tinea Versicolor: fungal imbalance, skin discoloration, and itching & scaling of the skin.

+As per various homeopathic materia medicas. These uses have not been evaluated by the FDA, and product has not been clinically tested.

Warnings

Warnings: If symptoms persit or worsen, discontinue use immediately and consult a healthcare professional.

If pregnant or breast-feeding, ask a health care professional before use.

Keep out of reach of children.

For external use only.

Avoid using near eyes or mouth.

If swallowed, get medical help or contact a Poison Control Center immediately.

Some individuals may be sensitive to essential oils. If irritation or reaction occurs, discontinue use.

Directions

Directions: Shake well before using.

Spray onto entire affected area and massage into skin twice daily.

Allow the spray to dry completely before putting on clothes.

Adults and children over 12 years of age.

OTHER SAFETY INFORMATION

Intended to complement, not replace, standard medical care.

Tamper resistant for your protection. Use only if safety seal is intact.

Inactive ingredients

Inactive ingredients: Apricot kernel oil, clove bud essential oil, lavender essential oil, lemongrass essential oil, tea tree essential oil.

Keep out of reach of children.

PREGNANCY OR BREAST FEEDING

If pregnant or breast-feeding, ask a healthcare professional before use.

HPUS* Active ingredients Purpose+

Equal volumes of each ingredient as follows:

Natrum carbonicum (30C)................................Scaling skin

Sulphur (6C).....................................................Itching

Tellurium metallicum (6C)................................Itchy, patchy skin